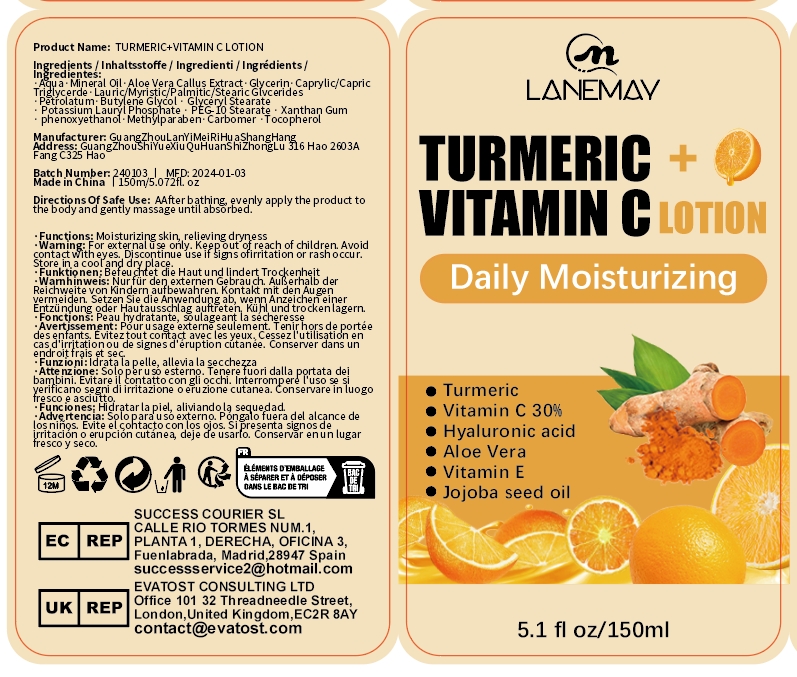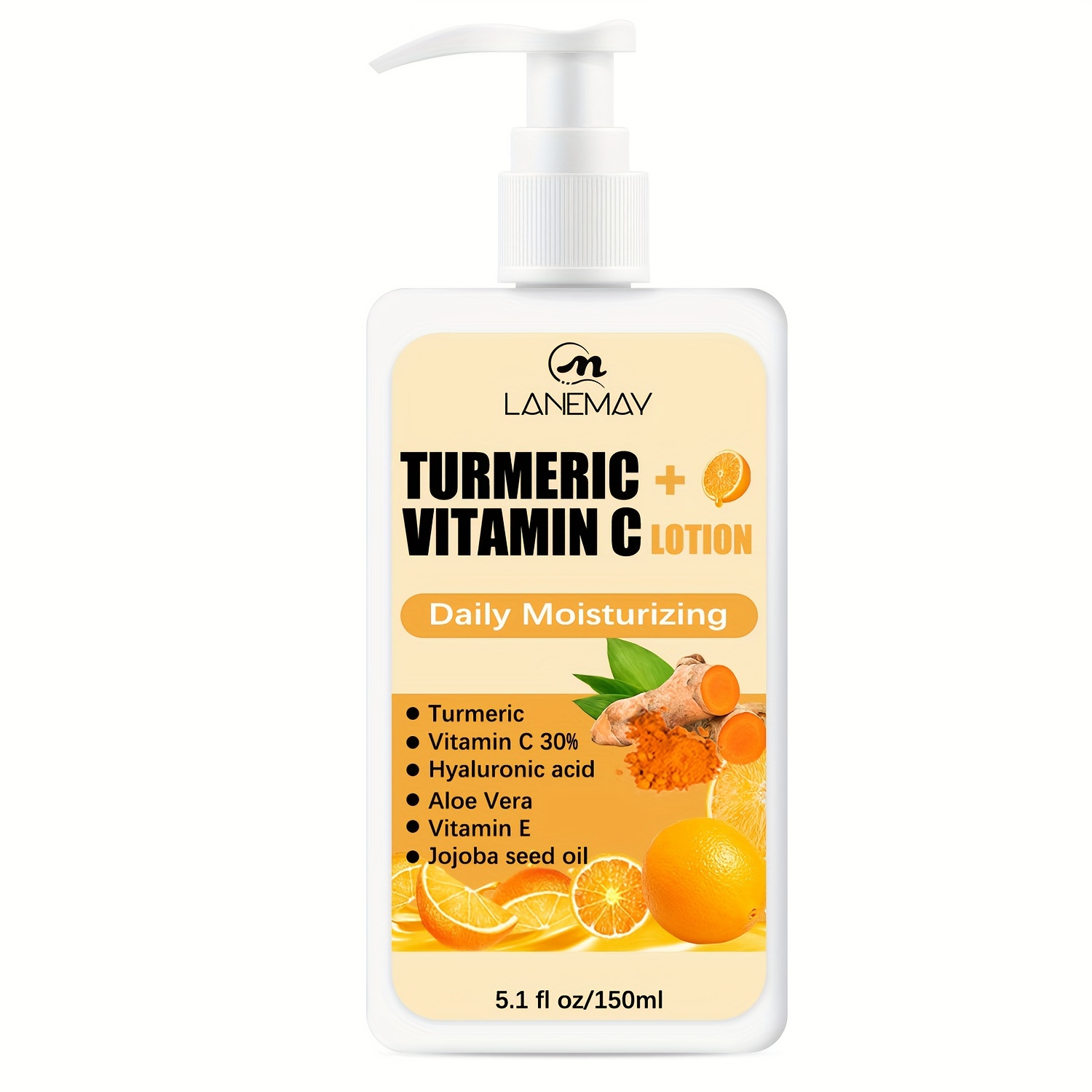 DRUG LABEL: Turmeric Vitamin C Cream
NDC: 84025-025 | Form: CREAM
Manufacturer: Guangzhou Yanxi Biotechnology Co., Ltd
Category: otc | Type: HUMAN OTC DRUG LABEL
Date: 20240330

ACTIVE INGREDIENTS: GLYCERIN 5 mg/50 mL; MINERAL OIL 5 mg/50 mL
INACTIVE INGREDIENTS: WATER

DOSAGE AND ADMINISTRATION

use for body or face

WARNINGS

For external use only.

INACTIVE INGREDIENT

aqua

INDICATIONS AND USAGE

apply the product to the skin

Keep out of reach of children.

PURPOSE

Moisturizing skin, relieving dryness